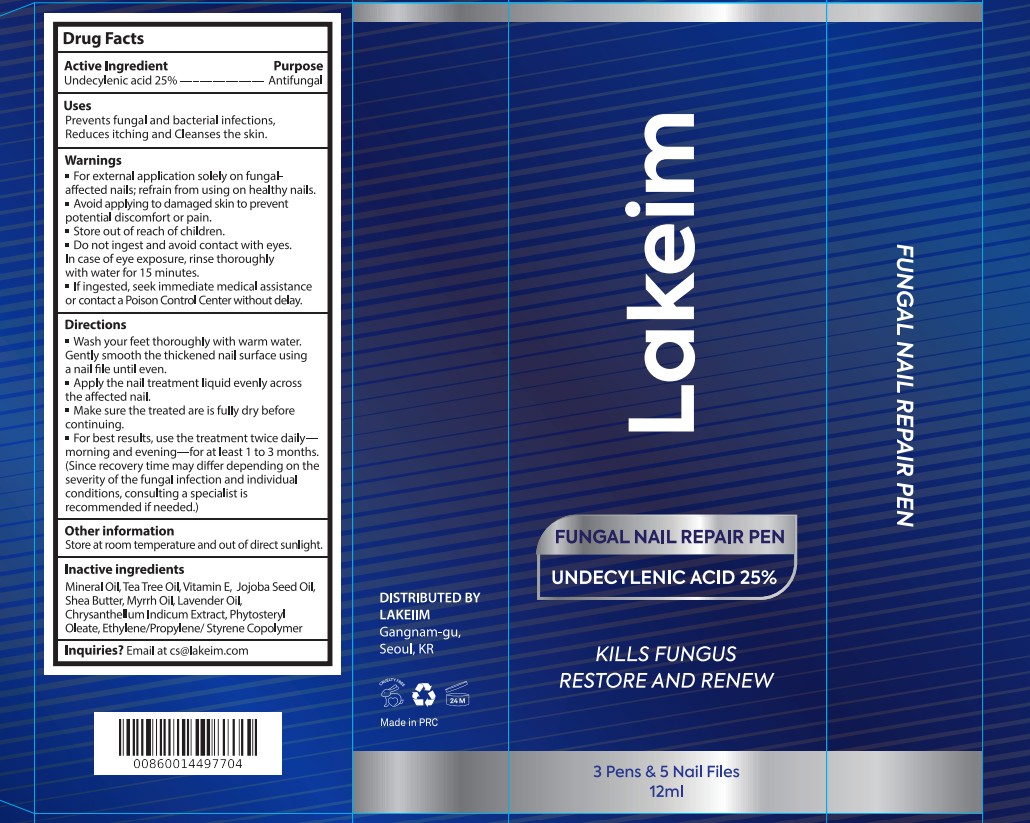 DRUG LABEL: Lakeim Fungal Nail Repair Pen
NDC: 87408-007 | Form: LIQUID
Manufacturer: Guangzhou Jingliang Cosmetics Co., Ltd.
Category: otc | Type: HUMAN OTC DRUG LABEL
Date: 20260218

ACTIVE INGREDIENTS: UNDECYLENIC ACID 25 g/100 mL
INACTIVE INGREDIENTS: JOJOBA OIL; MINERAL OIL; LAVENDER OIL; TOCOPHEROL; TEA TREE OIL; MYRRH OIL; .ALPHA.-METHYLENE BUTYROLACTONE; SHEA BUTTER; CHRYSANTHELLUM INDICUM FLOWER OIL; .BETA.-SITOSTERYL OLEATE

Active Ingredient

Active ingredient: Undecylenic Acid 25%

Ask Doctor

if irritation or symptoms worsen or last for more than 4 weeks.

Do not use

• If you are pregnant or breastfeeding
• your skin is injured or cracked.
• you are under 18 years of age.
• irritation or discomfort occurs.
• you are using other medicines on your nails.

Keep Oot Of Reach Of Children

Store out of reach of children

Purpose

Antifungal

Stop Use

if irritation or symptoms worsen or last for more than 4 weeks.

When Using

Avoid making eye contact. In case of accidental eye contact, flush eyes with copious amounts of cold tap water.

Avoid applying to damaged skin to prevent potential discomfort or pain

Inactive ingredients

Mineral Oil, Tea Tree Oil, Vitamin E, Jojoba Seed Oil, Shea Butter, Myrrh, Lavender Oil, Chrysanthellum Indicum Extract, Phytosteryl Oleate, Ethylene/Propylene/Styrene Copolymer

Directions

Wash your feet thoroughly with warm water.

Gently smooth the thickened nail surface using a nail file until even

Apply the nail treatment liquid evenly across the affected nail.

Make sure the treated area is fully dry before continuing

For best results, use the treatment twice daily morning and evening for at least 1 to 3 months

Since recovery time may differ depending on the severity of the fungal infection and individual conditions, consulting a specialist is recommended if needed

Warnings

For external application solely on fungal-affected nails, refrain from using on healthy nails

Avoid applying to damaged skin to prevent potential discomfort or pain

Store out of reach of children

Do not ingest and avoid contact with eyes.

In case of eye exposure, rinse thoroughly with water for 15 minutes

If ingested, seek immediate medical assistance or contact a Poison Control Center without delay.

Uses

Prevents fungal and bacterial infections.

Reduces itching and Cleanses the skin.

PACKAGE LABEL

Product Name: Lakeim Nail Fungus Repair Pen

Net Contents:

4 ml/ pen
3 pens in 1 PACKAGE